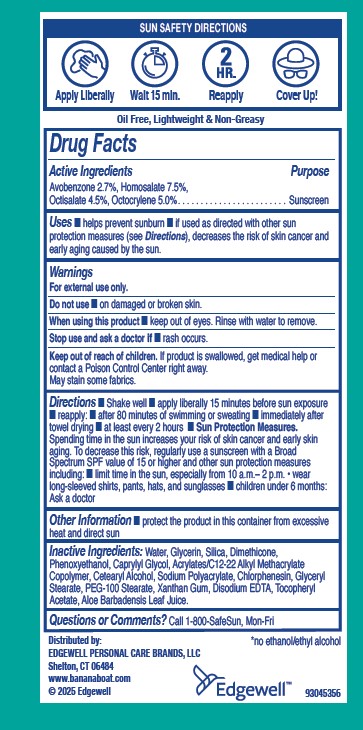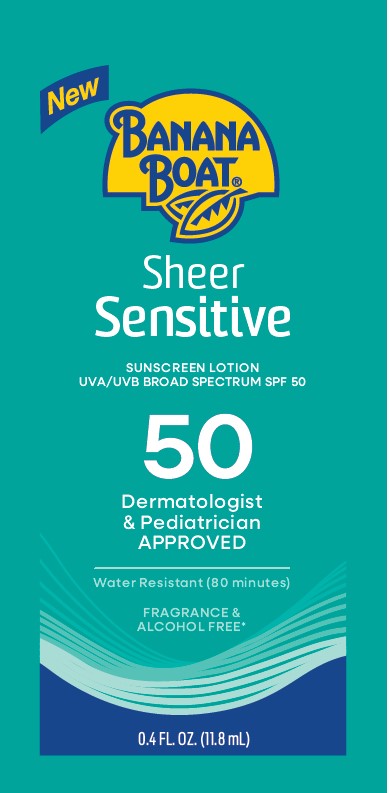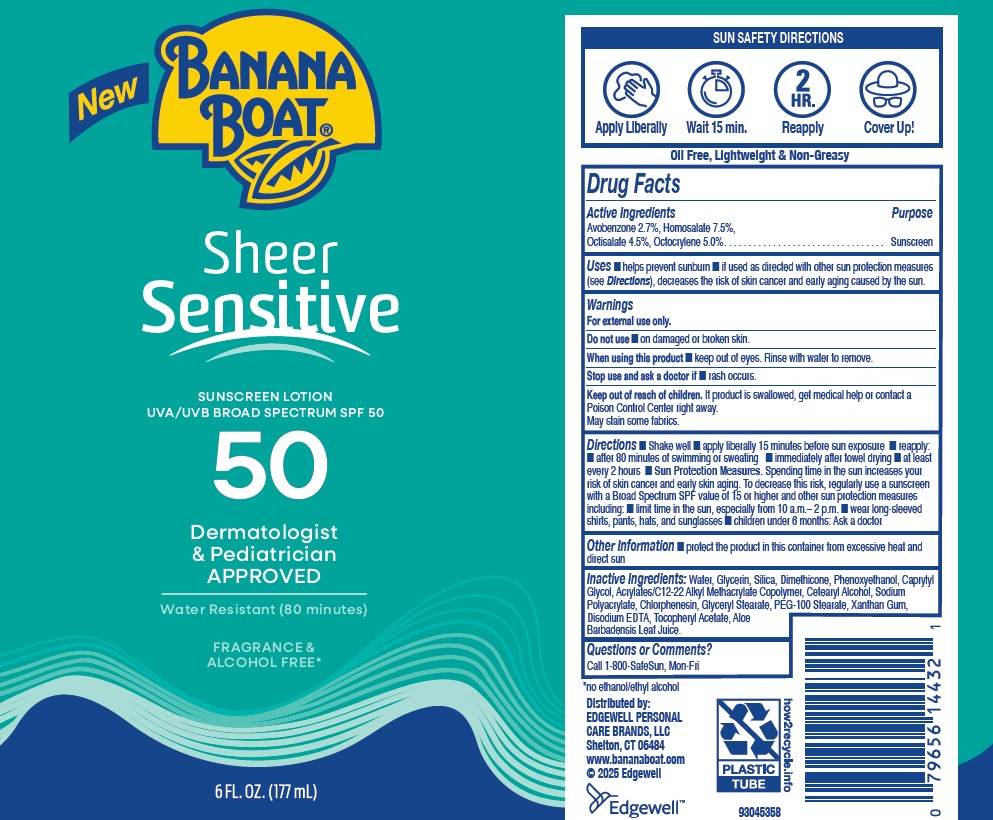 DRUG LABEL: BANANA BOAT
NDC: 63354-312 | Form: LOTION
Manufacturer: Edgewell Personal Care Brands LLC
Category: otc | Type: HUMAN OTC DRUG LABEL
Date: 20251202

ACTIVE INGREDIENTS: HOMOSALATE 7.5 g/100 g; AVOBENZONE 2.7 g/100 g; OCTOCRYLENE 5 g/100 g; OCTISALATE 4.5 g/100 g
INACTIVE INGREDIENTS: PEG-100 STEARATE; PHENOXYETHANOL; CAPRYLYL GLYCOL; CHLORPHENESIN; ALPHA-TOCOPHEROL ACETATE; GLYCERYL STEARATE; GLYCERIN; CETEARYL ALCOHOL; SODIUM POLYACRYLATE (2500000 MW); SILICA; ALOE BARBADENSIS LEAF; XANTHAN GUM; EDETATE DISODIUM; WATER; DIMETHICONE

Active Ingredients

Avobenzone 2.7%, Homosalate 7.5%,Octisalate 4.5%, Octocrylene 5.0%

Purpose

Sunscreen

Uses

■ helps prevent sunburn ■ if used as directed with other sun protection measures (see Directions), decreases the risk of skin cancer and early aging caused by the sun.

Warnings

For external use only.

May stain some fabrics.

Do not use

■ on damaged or broken skin.

When using this product

■ keep out of eyes. Rinse with water to remove.

Stop use and ask a doctor if

■ rash occurs.

Keep out of reach of children.

If product is swallowed, get medical help or contact a Poison Control Center right away.

Directions

■ Shake well ■ apply liberally 15 minutes before sun exposure ■ reapply: ■ after 80 minutes of swimming or sweating ■ immediately after towel drying ■ at least every 2 hours ■ Sun Protection Measures. Spending time in the sun increases your risk of skin cancer and early skin aging. To decrease this risk, regularly use a sunscreen with a Broad Spectrum SPF value of 15 or higher and other sun protection measures including: ■ limit time in the sun, especially from 10 a.m.– 2 p.m. ■ wear long-sleeved shirts, pants, hats, and sunglasses ■ children under 6 months: Ask a doctor

Other Information

■ protect the product in this container from excessive heat and direct sun

Inactive Ingredients:

Water, Glycerin, Silica, Dimethicone, Phenoxyethanol, Caprylyl Glycol, Acrylates/C12‐22 Alkyl Methacrylate Copolymer, Cetearyl Alcohol, Sodium Polyacrylate, Chlorphenesin, Glyceryl Stearate, PEG‐100 Stearate, Xanthan Gum, Disodium EDTA, Tocopheryl Acetate, Aloe Barbadensis Leaf Juice.

Questions or Comments?

Call 1-800-SafeSun, Mon-Fr

Principal Display Panel

New

BANANA BOAT

Sheer

Sensitive

SUNSCREEN LOTION

UVA/UVB BROAD SPECTRUM SPF 50

50

Dermatologist

& Pediatrician

APPROVED

Water Resistant (80 minutes)

FRAGRANCE &

ALCOHOL FREE

6 FL. OZ. (177mL)

New

BANANA BOAT

Sheer

Sensitive

SUNSCREEN LOTION

UVA/UVB BROAD SPECTRUM SPF 50

50

Dermatologist

& Pediatrician

APPROVED

Water Resistant (80 minutes)

FRAGRANCE &

ALCOHOL FREE

0.4 FL. OZ. (11.8mL)